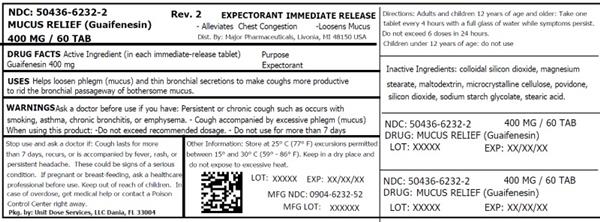 DRUG LABEL: MUCOSA
NDC: 50436-6232 | Form: TABLET
Manufacturer: Unit Dose Services
Category: otc | Type: HUMAN OTC DRUG LABEL
Date: 20170719

ACTIVE INGREDIENTS: GUAIFENESIN 400 mg/1 1
INACTIVE INGREDIENTS: SILICON DIOXIDE; MAGNESIUM STEARATE; MALTODEXTRIN; MICROCRYSTALLINE CELLULOSE; POVIDONE, UNSPECIFIED; SODIUM STARCH GLYCOLATE TYPE A POTATO; STEARIC ACID

ACTIVE INGREDIENT

Each immediate release tablet contains: Guaifenesin 400 mg

PURPOSE: EXPECTORANT

Keep Out of Reach of Children: In case of overdose, get medical help or contact a Poison Control Center

INACTIVE INGREDIENT

Silicon Dioxide, Magnesium Stearate, Maltodextrin, Cellulose, Microcrystalline, Povidone, Sodium Starch Glycolate, Stearic Acid

DOSAGE AND ADMINISTRATION

Adults and children 12 years of age and older, take 1 tablet every 4 hours with a full glass of water while symptoms persist. Do not exceed 6 doses in 24 hours. Children under 12 years of age do not use

INDICATIONS AND USAGE

Helps loosen phlegm (mucus) and thin

bronchial secretions to make coughts more productive to rid the bronchial passageway of bothersome mucus.

Ask a doctor berfoe use if you have: Persistent or chronic cough such as occurs with smoking, asthma, chronic bronchitis, or emphysema; Cough accompanied by excessive phlegm (mucus)

HOW SUPPLIED

Product: 50436-6232

NDC: 50436-6232-2 60 TABLET in a BOTTLE